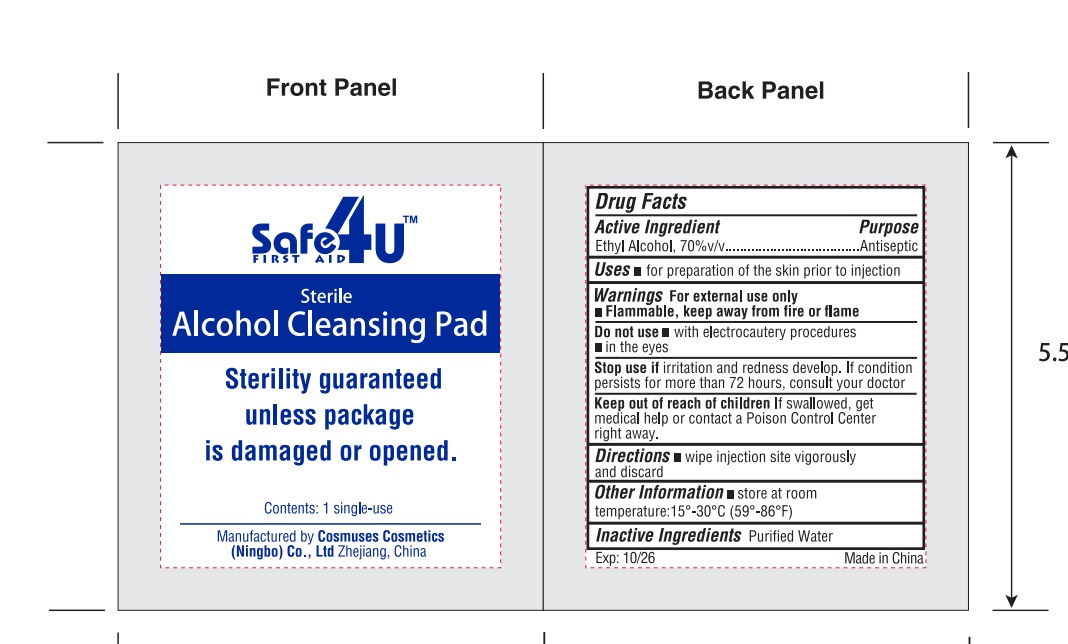 DRUG LABEL: alcohol pad
NDC: 82953-012 | Form: CLOTH
Manufacturer: Cosmuses Cosmetics (Ningbo) Co., Ltd.
Category: otc | Type: HUMAN OTC DRUG LABEL
Date: 20241204

ACTIVE INGREDIENTS: ALCOHOL 0.7 mL/1 1
INACTIVE INGREDIENTS: WATER

alcohol pad

Drug Fact

Active Ingredient

Ethyl alcohol 70% v/v

Purpose

Antiseptic

Uses

for preparation of the skin prior to injection.

Warnings

- For external use only.
- Flammable, keep away from fire or flame.

Do not use

- with electrocautery procedures.
- in the eyes.

Stop use if irritation and redness develop. If condition persists for more than 72 hours, consult your doctor.

Keep out of reach of children if swallowed, get medical help or contact a poison control center right away.

Directions

Wipe injection site vigorously and discard.

Inactive Ingredients

Purified Water

other information

store at room temperature: 15℃-30℃ (59℉-86℉)